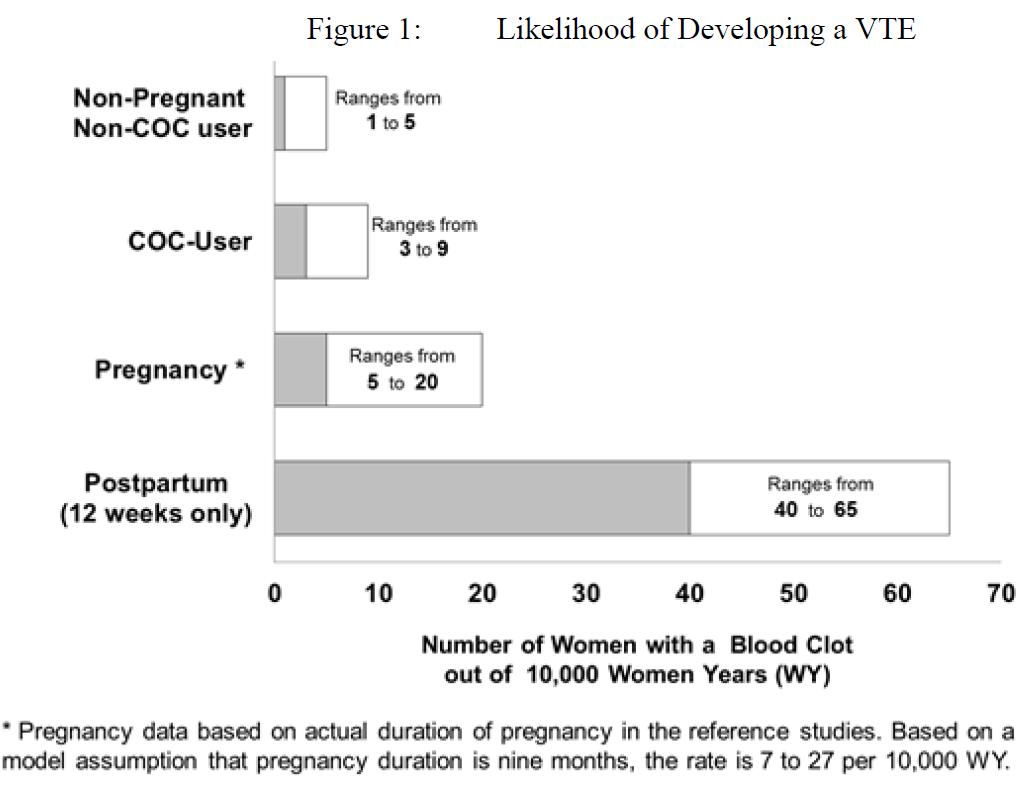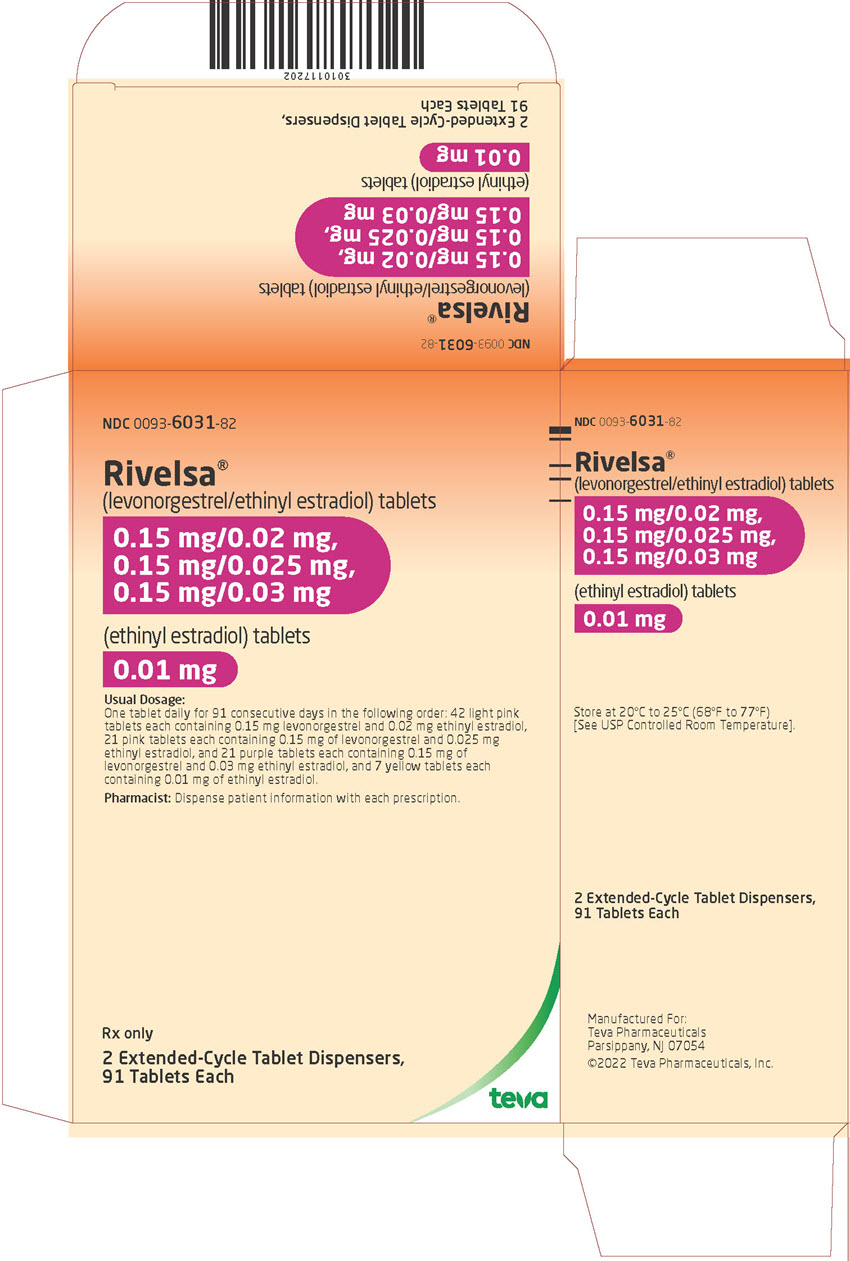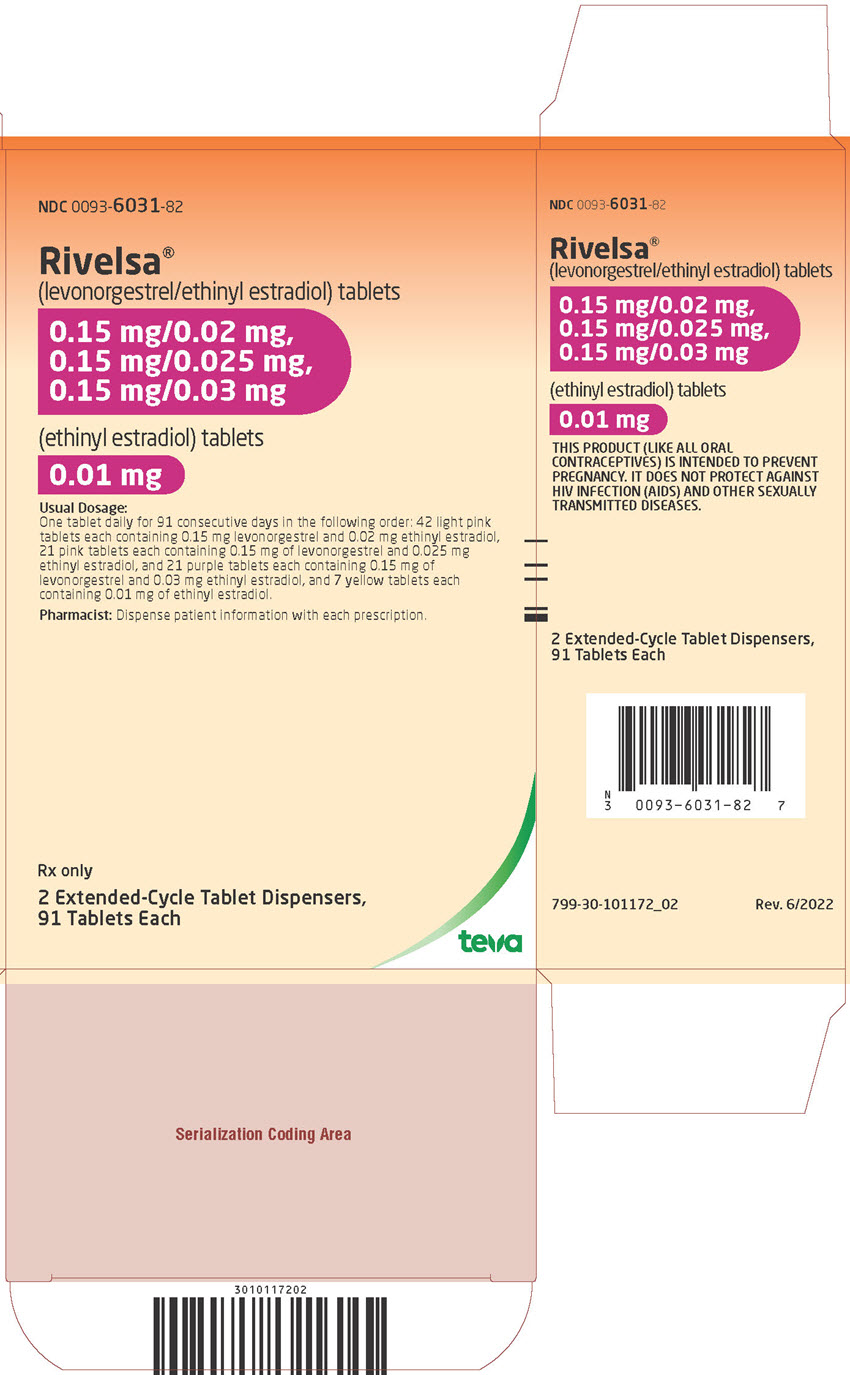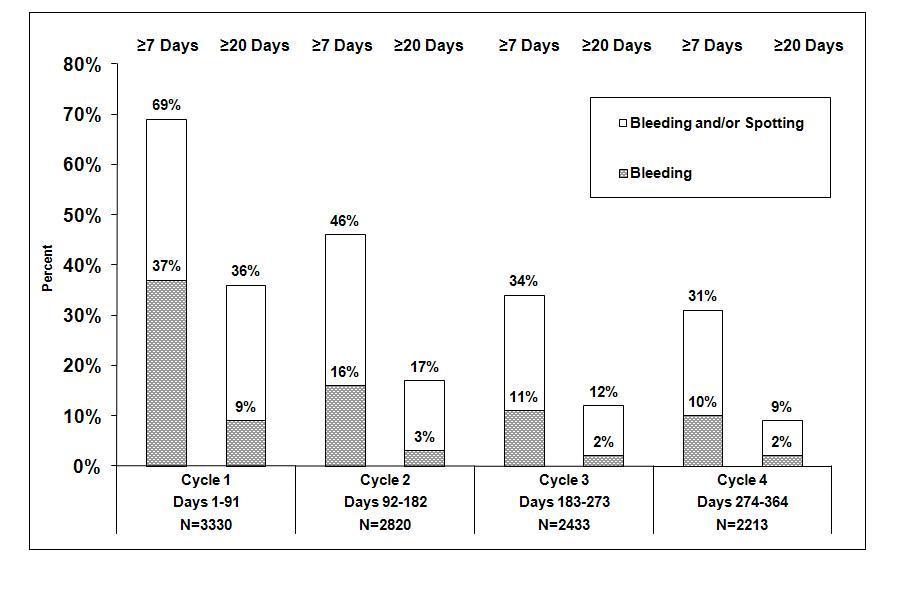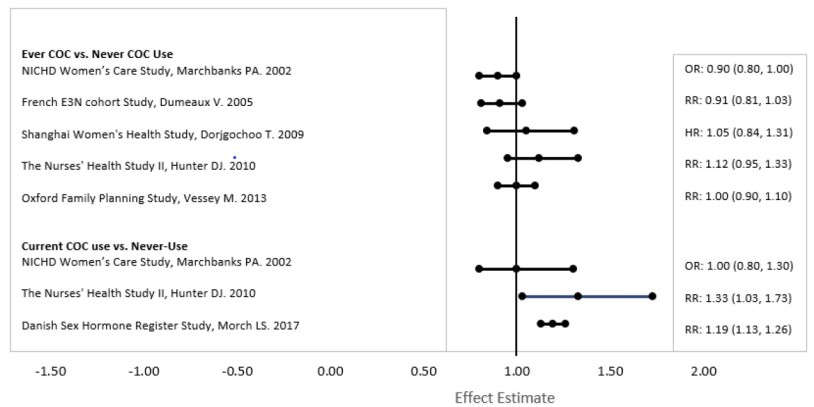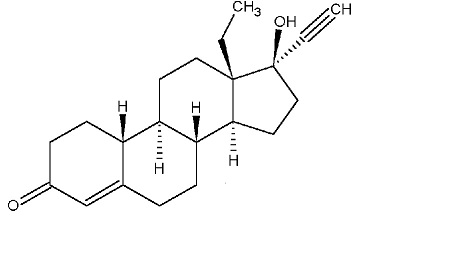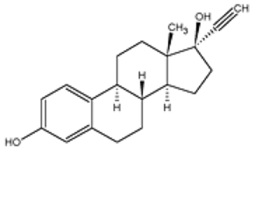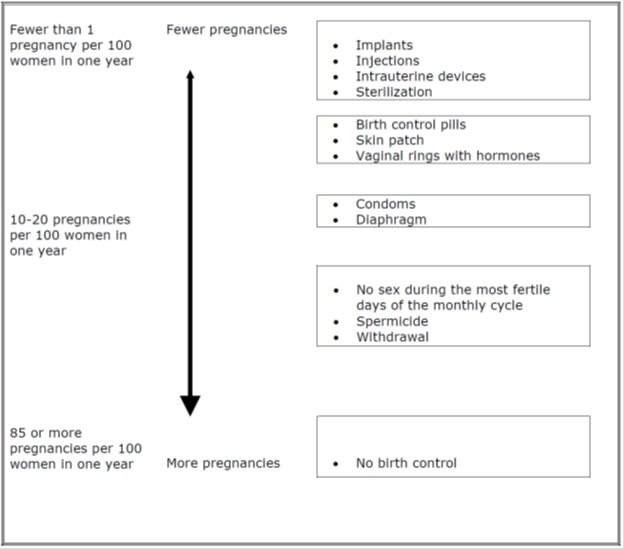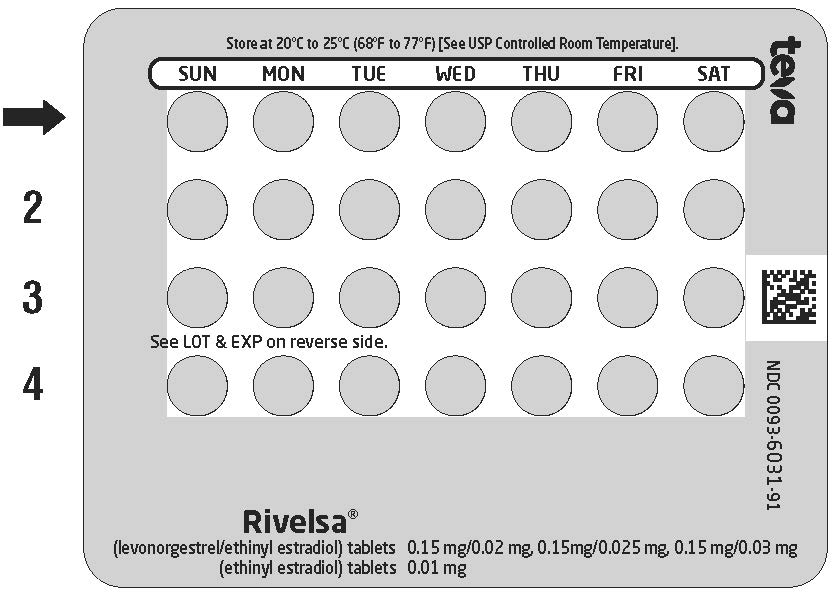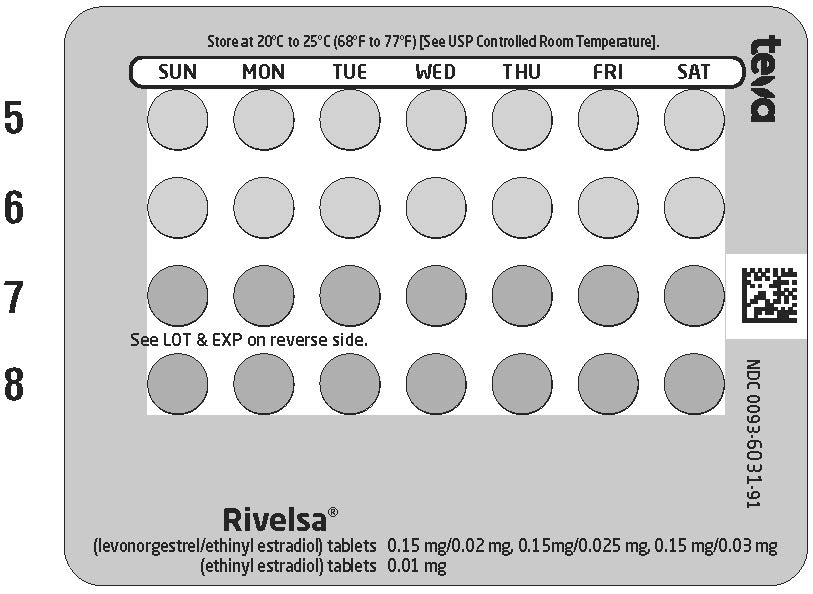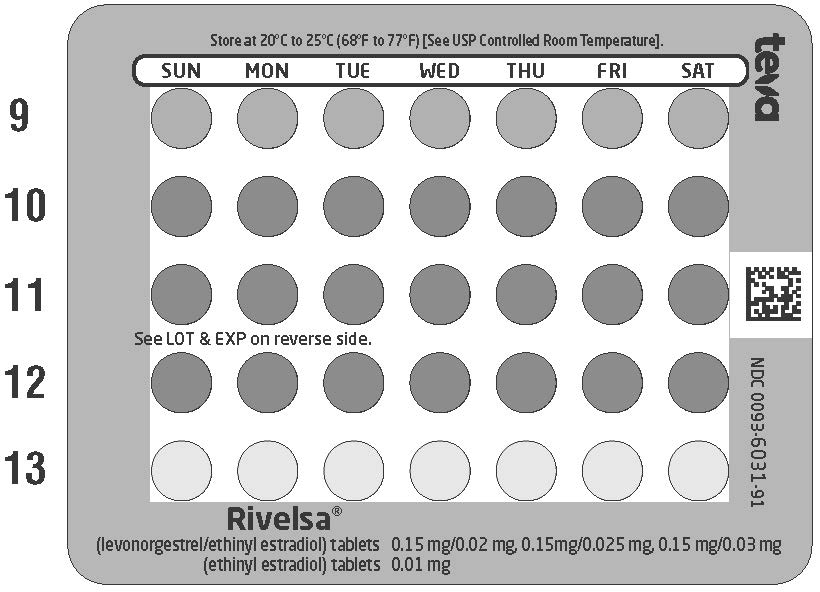 DRUG LABEL: Rivelsa
NDC: 0093-6031 | Form: KIT | Route: ORAL
Manufacturer: Teva Pharmaceuticals USA, Inc.
Category: prescription | Type: HUMAN PRESCRIPTION DRUG LABEL
Date: 20241022

ACTIVE INGREDIENTS: LEVONORGESTREL 0.15 mg/1 1; ETHINYL ESTRADIOL 0.02 mg/1 1; LEVONORGESTREL 0.15 mg/1 1; ETHINYL ESTRADIOL 0.025 mg/1 1; LEVONORGESTREL 0.15 mg/1 1; ETHINYL ESTRADIOL 0.03 mg/1 1; ETHINYL ESTRADIOL 0.01 mg/1 1
INACTIVE INGREDIENTS: ANHYDROUS LACTOSE; D&C RED NO. 27; FD&C BLUE NO. 2; INDIGOTINDISULFONATE SODIUM; FD&C YELLOW NO. 6; HYPROMELLOSE 2208 (3 MPA.S); HYPROMELLOSE, UNSPECIFIED; LACTOSE MONOHYDRATE; MICROCRYSTALLINE CELLULOSE; MAGNESIUM STEARATE; POLYETHYLENE GLYCOL, UNSPECIFIED; TITANIUM DIOXIDE; TRIACETIN; ANHYDROUS LACTOSE; D&C RED NO. 27; FD&C BLUE NO. 2; INDIGOTINDISULFONATE SODIUM; HYPROMELLOSE 2208 (3 MPA.S); HYPROMELLOSE, UNSPECIFIED; LACTOSE MONOHYDRATE; MICROCRYSTALLINE CELLULOSE; MAGNESIUM STEARATE; POLYETHYLENE GLYCOL, UNSPECIFIED; TITANIUM DIOXIDE; TRIACETIN; ANHYDROUS LACTOSE; D&C RED NO. 27; FD&C BLUE NO. 1; HYPROMELLOSE 2208 (3 MPA.S); HYPROMELLOSE, UNSPECIFIED; LACTOSE MONOHYDRATE; MICROCRYSTALLINE CELLULOSE; MAGNESIUM STEARATE; POLYETHYLENE GLYCOL, UNSPECIFIED; TITANIUM DIOXIDE; TRIACETIN; ANHYDROUS LACTOSE; D&C YELLOW NO. 10; FD&C YELLOW NO. 6; HYPROMELLOSE 2910 (3 MPA.S); HYPROMELLOSE 2910 (6 MPA.S); MAGNESIUM STEARATE; MICROCRYSTALLINE CELLULOSE; POLACRILIN POTASSIUM; POLYETHYLENE GLYCOL 400; POLYSORBATE 80; TITANIUM DIOXIDE

HIGHLIGHTS OF PRESCRIBING INFORMATION

These highlights do not include all the information needed to use RIVELSA safely and effectively. See full prescribing information for RIVELSA.
RIVELSA® (levonorgestrel/ethinyl estradiol and ethinyl estradiol) tablets, for oral use
Initial U.S. Approval: 1982

WARNING: CIGARETTE SMOKING AND SERIOUS CARDIOVASCULAR EVENTS

See full prescribing information for complete boxed warning.

- RIVELSA is contraindicated in women over 35 years old who smoke. (4)
- Cigarette smoking increases the risk of serious cardiovascular events from combination oral contraceptive (COC) use. (4)

1 INDICATIONS AND USAGE

RIVELSA is a combination of levonorgestrel, a progestin, and ethinyl estradiol, an estrogen, indicated for use by females of reproductive potential to prevent pregnancy. (1)

2 DOSAGE AND ADMINISTRATION

- Take one tablet daily by mouth at the same time every day for 91 days in the order directed on the blister pack. (2)

3 DOSAGE FORMS AND STRENGTHS

RIVELSA consists of 91 tablets in the following order (3):

- 42 light pink tablets containing 0.15 mg levonorgestrel and 0.02 mg ethinyl estradiol,
- 21 pink tablets containing 0.15 mg of levonorgestrel and 0.025 mg ethinyl estradiol, and
- 21 purple tablets containing 0.15 mg of levonorgestrel and 0.03 mg ethinyl estradiol, and
- 7 yellow tablets containing 0.01 mg of ethinyl estradiol.

4 CONTRAINDICATIONS

- A high risk of arterial or venous thrombotic diseases (4)
- Undiagnosed abnormal uterine bleeding (4)
- Breast cancer (4)
- Liver tumors or liver disease (4)
- Co-administration with Hepatitis C drug combinations containing ombitasvir/paritaprevir/ritonavir, with or without dasabuvir (4)

5 WARNINGS AND PRECAUTIONS

- Vascular risks: Stop if a thrombotic or thromboembolic event occurs. Stop at least 4 weeks before and through 2 weeks after major surgery. Start no earlier than 4 weeks after delivery, in women who are not breastfeeding. Consider cardiovascular risk factors before initiating in all females, particularly those over 35 years. (5.1, 5.5)
- Liver disease: Discontinue if jaundice occurs. (5.2)
- Hypertension: If used in females with well-controlled hypertension, monitor blood pressure and stop use if blood pressure rises significantly. (5.3)
- Gallbladder disease: May cause or worsen gallbladder disease. (5.6)
- Carbohydrate and lipid metabolic effects: Monitor glucose in prediabetic and diabetic women taking RIVELSA. Consider an alternate contraceptive method for women with uncontrolled dyslipidemias. (5.7)
- Headache: Evaluate significant change in headaches and discontinue if indicated. (5.8)
- Uterine bleeding: May cause irregular bleeding or amenorrhea. Evaluate for other causes if symptoms persist. (5.9)

6 ADVERSE REACTIONS

The most common adverse reactions (≥2%) in clinical trials for RIVELSA were headaches, heavy/irregular vaginal bleeding, nausea/vomiting, acne, dysmenorrhea, weight increased, mood changes, anxiety/panic attack, breast pain and migraines. (6)

To report SUSPECTED ADVERSE REACTIONS, contact Teva Pharmaceuticals at 1-888-483-8279 or FDA at 1-800-FDA-1088 or www.fda.gov/medwatch.

7 DRUG INTERACTIONS

Enzyme inducers (e.g., CYP3A4): May decrease the effectiveness of RIVELSA or increase breakthrough bleeding. Counsel patients to use a backup or alternative method of contraception when enzyme inducers are used with RIVELSA. (7.1)

8 USE IN SPECIFIC POPULATIONS

- Pregnancy: Discontinue use if pregnancy occurs. (8.1)
- Lactation: Advise use of another method. RIVELSA is not recommended for nursing mothers; may decrease milk production. (8.2)

FULL PRESCRIBING INFORMATION

WARNING: CIGARETTE SMOKING AND SERIOUS CARDIOVASCULAR EVENTS

Cigarette smoking increases the risk of serious cardiovascular events from combination oral contraceptives (COC) use. This risk increases with age, particularly in women over 35 years of age, and with the number of cigarettes smoked. For this reason, COCs, including RIVELSA, are contraindicated in women who are over 35 years of age and smoke [see Contraindications (4) and Warnings and Precautions (5.1)].

1 INDICATIONS AND USAGE

RIVELSA® is indicated for use by females of reproductive age to prevent pregnancy.

2 DOSAGE AND ADMINISTRATION

2.1 How to Start and Take RIVELSA

Begin RIVELSA on the first Sunday after the onset of menstruation. If menstruation begins on a Sunday, take the first light pink tablet that day.

For each 91-day course, take in the following order:

1. Start the first light pink tablet on the first Sunday after the onset of menstruation. If menstruation begins on a Sunday, take the tablet on that day. Then take one light pink tablet once daily for a total of 42 consecutive days. Use a non-hormonal backup method of contraception (such as condoms and spermicide) for the first 7 days of treatment.
2. One pink tablet once daily for 21 consecutive days.
3. One purple tablet once daily for 21 days.
4. One yellow tablet once daily for 7 days. Bleeding should occur during yellow tablet use.

Begin the next and all subsequent 91-day courses of RIVELSA without interruption on the same day of the week (Sunday) on which the first dose of RIVELSA was taken. Follow the same schedule as the initial 91-day course: light pink tablet once daily for 42 days, pink tablet once daily for 21 days, purple tablet once daily for 21 days, and yellow tablet once daily for 7 days. If the next pill pack is not started immediately, use a non-hormonal backup method of contraception until a light pink tablet has been taken once daily for 7 consecutive days.

Switching to RIVELSA from another oral hormonal contraceptive or from another contraceptive method (transdermal patch, vaginal ring, injection, intrauterine contraceptive, implant)

Start on the Sunday after the patient’s next period starts. Use additional non-hormonal contraceptive (such as condoms and spermicide) until the patient has taken 7 light pink pills (7 days).

Starting RIVELSA after Abortion or Miscarriage

First-trimester

RIVELSA may be started on the Sunday after an abortion or miscarriage. The patient must use additional non-hormonal contraception (such as condoms and spermicide) until the patient has taken a light pink tablet for 7 days.

Second-trimester

Do not start until 4 weeks after a second-trimester abortion or miscarriage, due to the increased risk of thromboembolic disease. Start contraceptive therapy with RIVELSA following the instructions for women not currently using hormonal contraception. Use additional non-hormonal contraception (such as condoms and spermicide) until the patient has taken a light pink tablet for 7 days [see Contraindications (4) and Warnings and Precautions (5.1)].

Starting RIVELSA after Childbirth

Do not start until 4 weeks after delivery, due to the increased risk of thromboembolic disease. Start contraceptive therapy with RIVELSA following the instructions for women not currently using hormonal contraception. Use additional non-hormonal contraception (such as condoms and spermicide) until the patient has taken a light pink tablet for 7 days [see Contraindications (4) and Warnings and Precautions (5.1)].

RIVELSA is not recommended for use in lactating women [see Use in Specific Populations (8.2)].

If the woman has not yet had a period postpartum, consider the possibility of ovulation and conception occurring prior to use of RIVELSA [see Warnings and Precautions (5.1), Use in Specific Populations (8.1)].

2.2 Dosing RIVELSA

Take one tablet by mouth at the same time every day. The dosage of RIVELSA is one light pink tablet once daily for 42 days, one pink tablet once daily for 21 days, one purple tablet once daily for 21 days, and one yellow tablet once daily for 7 days.

To achieve maximum contraceptive effectiveness, take RIVELSA exactly as directed, in the order directed, and at intervals not exceeding 24 hours. The failure rate may increase when pills are missed or taken incorrectly.

2.3 Missed Doses

Table 1. Instructions for Missed RIVELSA Tablets

If one light pink, pink or purple tablet is missed | Take the missed tablet as soon as possible. Take the next tablet at the regular time. Continue taking one tablet a day until the pack is finished. A backup birth control method is not required if the patient has sex.
If two light pink, pink or purple tablets in a row are missed | Take the two missed tablets as soon as possible, and the next two tablets the next day. Continue taking one tablet a day until the pack is finished. Use additional nonhormonal contraception (such as condoms and spermicide) until tablets have been taken for 7 days after missing tablets.
If three or more light pink, pink or purple tablets in a row are missed | Throw away the missed tablets. Continue taking one tablet every day as indicated on the pack until the pack is finished. Bleeding may occur during the week following the missed tablets. Use additional nonhormonal contraception (such as condoms and spermicide) until tablets have been taken for 7 days after missing tablets.
If any of the seven yellow tablets are missed | Throw away the missed tablets. Continue taking the remaining tablets until the pack is finished. A backup birth control method is not needed.

2.4 Advice in Case of Gastrointestinal Disturbances

In case of severe vomiting or diarrhea, absorption may not be complete and additional contraceptive measures should be taken. If vomiting or diarrhea occurs within 3-4 hours after taking a light pink, pink or purple tablet, handle this as a missed tablet [see Dosage and Administration (2.3)].

3 DOSAGE FORMS AND STRENGTHS

RIVELSA (levonorgestrel/ethinyl estradiol and ethinyl estradiol) tablets are available as round, film-coated, biconvex tablets debossed with TV on one side, packaged in Extended-Cycle Tablet Dispensers, each containing a 13-week supply of tablets in the following order:

- 42 light pink tablets, each containing 0.15 mg of levonorgestrel and 0.02 mg ethinyl estradiol: debossed with 076 on the other side
- 21 pink tablets containing 0.15 mg of levonorgestrel and 0.025 mg ethinyl estradiol: debossed with 075 on the other side
- 21 purple tablets containing 0.15 mg of levonorgestrel and 0.03 mg ethinyl estradiol: debossed with 074 on the other side and
- 7 yellow tablets containing 0.01 mg of ethinyl estradiol: debossed with 077 on the other side

4 CONTRAINDICATIONS

RIVELSA is contraindicated in females who are known to have or develop the following conditions:

- A high risk of arterial or venous thrombotic diseases. Examples include females who are known to:
  - Smoke, if over age 35 [see Boxed Warning and Warnings and Precautions (5.1)].
  - Have current or history of deep vein thrombosis or pulmonary embolism [see Warnings and Precautions (5.1)].
  - Have cerebrovascular disease [see Warnings and Precautions (5.1)].
  - Have coronary artery disease [see Warnings and Precautions (5.1)].
  - Have thrombogenic valvular or thrombogenic rhythm diseases of the heart (for example, subacute bacterial endocarditis with valvular disease, or atrial fibrillation) [see Warnings and Precautions (5.1)].
  - Have inherited or acquired hypercoagulopathies [see Warnings and Precautions (5.1)].
  - Have uncontrolled hypertension or hypertension with vascular disease [see Warnings and Precautions (5.5)].
  - Have diabetes mellitus and are over age 35, diabetes mellitus with hypertension or with vascular disease or other end-organ damage, or diabetes mellitus of > 20 years duration [see Warnings and Precautions (5.7)].
  - Have headaches with focal neurological symptoms, migraine headaches with aura, or over age 35 with any migraine headaches [see Warnings and Precautions (5.8)].

- Current diagnosis of, or history of, breast cancer, which may be hormone sensitive [see Warnings and Precautions (5.11)].
- Liver tumors, acute viral hepatitis, or severe (decompensated) cirrhosis [see Warnings and Precautions (5.2) and Use in Specific Populations (8.6)].
- Undiagnosed abnormal uterine bleeding [see Warnings and Precautions (5.9)].
- Use of Hepatitis C drug combinations containing ombitasvir/paritaprevir/ritonavir, with or without dasabuvir, due to the potential for ALT elevations [see Warnings and Precautions (5.4)].

5 WARNINGS AND PRECAUTIONS

5.1 Thromboembolic Disorders and Other Vascular Conditions

- Stop RIVELSA if an arterial or deep venous thromboembolic event occurs.
- Stop RIVELSA if there is unexplained loss of vision, proptosis, diplopia, papilledema, or retinal vascular lesions. Evaluate for retinal vein thrombosis immediately.
- Discontinue RIVELSA during prolonged immobilization. If feasible, stop RIVELSA at least 4 weeks before and through 2 weeks after major surgery or other surgeries known to have an elevated risk of thromboembolism.
- Start RIVELSA no earlier than 4 weeks after delivery, in females who are not breastfeeding. The risk of postpartum thromboembolism decreases after the third postpartum week, whereas the risk of ovulation increases after the third postpartum week.
- Before starting RIVELSA evaluate any past medical history or family history of thrombotic or thromboembolic disorders and consider whether the history suggests an inherited or acquired hypercoagulopathy. RIVELSA is contraindicated in females with a high risk of arterial or venous/thromboembolic diseases [see Contraindications (4)].

Arterial Events

COCs increase the risk of cardiovascular events and cerebrovascular events, such as myocardial infarction and stroke. The risk is greater among older women (> 35 years of age), smokers, and females with hypertension, dyslipidemia, diabetes, or obesity.

RIVELSA is contraindicated in women over 35 years of age who smoke [see Contraindications (4)]. Cigarette smoking increases the risk of serious cardiovascular events from COC use. This risk increases with age, particularly in women over 35 years of age, and with the number of cigarettes smoked.

Venous Events

Use of COCs increases the risk of venous thromboembolic events (VTEs), such as deep vein thrombosis and pulmonary embolism. Risk factors for VTEs include smoking, obesity, and family history of VTE, in addition to other factors that contraindicate use of COCs [see Contraindications (4)]. While the increased risk of VTE associated with use of COCs is well-established, the rates of VTE are even greater during pregnancy, and especially during the postpartum period (see Figure 1). The rate of VTE in females using COCs has been estimated to be 3 to 9 cases per 10,000 woman years.

The risk of VTE is highest during the first year of use of a COC and when restarting hormonal contraception after a break of four weeks or longer. The risk of thromboembolic disease due to COCs gradually disappears after COC use is discontinued.

Figure 1 shows the risk of developing a VTE for females who are not pregnant and do not use oral contraceptives, for females who use oral contraceptives, and for females in the postpartum period. To put the risk of developing a VTE into perspective: If 10,000 females who are not pregnant and do not use oral contraceptives are followed for one year, between 1 and 5 of these females will develop a VTE.

Use of RIVELSA provides women with more hormonal exposure on a yearly basis than conventional monthly oral contraceptives containing the same strength synthetic estrogens and progestins (an additional 9 and 13 weeks of exposure to progestin and estrogen, respectively, per year). In the clinical trial, three cases of deep vein thrombosis were reported.

5.2 Liver Disease

Elevated Liver Enzymes

RIVELSA is contraindicated in females with acute viral hepatitis or severe (decompensated) cirrhosis of the liver [see Contraindications (4)]. Acute liver test abnormalities may necessitate the discontinuation of RIVELSA until liver tests return to normal and RIVELSA causation has been excluded. Discontinue RIVELSA if jaundice develops.

Liver Tumors

RIVELSA is contraindicated in females with benign or malignant liver tumors [see Contraindications (4)]. COCs increase the risk of hepatic adenomas. An estimate of the attributable risk is 3.3 cases/100,000 COC users. Rupture of hepatic adenomas may cause death from abdominal hemorrhage.

Studies have shown an increased risk of developing hepatocellular carcinoma in long-term (> 8 years) COC users. The attributable risk of liver cancers in COC users is less than one case per million users.

5.3 Hypertension

RIVELSA is contraindicated in women with uncontrolled hypertension or hypertension with vascular disease [see Contraindications (4)]. For all females, including those with well-controlled hypertension, monitor blood pressure at routine visits and stop RIVELSA if blood pressure rises significantly.

An increase in blood pressure has been reported in women taking COCs, and this increase is more likely in older women and with extended duration of use. The effect of COCs on blood pressure may vary according to the progestin in the COC.

5.4 Risk of Liver Enzyme Elevations with Concomitant Hepatitis C Treatment

During clinical trials with the Hepatitis C combination drug regimen that contains ombitasvir/paritaprevir/ritonavir, with or without dasabuvir, ALT elevations greater than 5 times the upper limit of normal (ULN), including some cases greater than 20 times the ULN, were significantly more frequent in women using ethinyl estradiol-containing medications, such as RIVELSA. Discontinue RIVELSA prior to starting therapy with the combination drug regimen ombitasvir/paritaprevir/ritonavir, with or without dasabuvir [see Contraindications (4)]. RIVELSA can be restarted approximately 2 weeks following completion of treatment with the Hepatitis C combination drug regimen.

5.5 Age-related Considerations

The risk for cardiovascular disease and prevalence of risk factors for cardiovascular disease increases with age. Certain conditions, such as smoking and migraine headache without aura, that do not contraindicate COC use in younger females, are contraindications to use in women over 35 years of age [see Contraindications (4) and Warnings and Precautions (5.1)]. Consider the presence of underlying risk factors that may increase the risk of cardiovascular disease or VTE, particularly before initiating RIVELSA for women over 35 years, such as:

- Hypertension
- Diabetes
- Dyslipidemia
- Obesity

5.6 Gallbladder Disease

Studies suggest a small increased relative risk of developing gallbladder disease among COC users. Use of COCs, including RIVELSA, may also worsen existing gallbladder disease.

A past history of COC-related cholestasis predicts an increased risk with subsequent COC use. Women with a history of pregnancy-related cholestasis may be at an increased risk for COC-related cholestasis.

5.7 Adverse Carbohydrate and Lipid Metabolic Effects

Hyperglycemia

RIVELSA is contraindicated in diabetic women over age 35, or females who have diabetes with hypertension, nephropathy, retinopathy, neuropathy, other vascular disease, or females with diabetes of > 20 years duration [see Contraindications (4)]. RIVELSA may decrease glucose tolerance. Carefully monitor prediabetic and diabetic females who are taking RIVELSA.

Dyslipidemia

Consider alternative contraception for females with uncontrolled dyslipidemias. RIVELSA may cause adverse lipid changes.

Females with hypertriglyceridemia, or a family history thereof, may have an increase in serum triglyceride concentrations when using RIVELSA, which may increase the risk of pancreatitis.

5.8 Headache

RIVELSA is contraindicated in females who have headaches with focal neurological symptoms or have migraine headaches with aura, and in women over 35 years of age who have migraine headaches with or without aura [see Contraindications (4)].

If a woman taking RIVELSA develops new headaches that are recurrent, persistent, or severe, evaluate the cause and discontinue RIVELSA if indicated.

Consider discontinuation of RIVELSA in the case of increased frequency or severity of migraine during COC use (which may be prodromal of a cerebrovascular event) [see Contraindications (4)].

5.9 Bleeding Irregularities and Amenorrhea

Bleeding and/or spotting that occurs at any time while taking the first 84 tablets (light pink, pink and purple) of each extended-cycle regimen is considered “unscheduled” bleeding/spotting. Bleeding that occurs during the time a woman takes the seven tablets (yellow) containing 10 mcg of ethinyl estradiol is considered “scheduled” bleeding.

Unscheduled and Scheduled Bleeding and Spotting

Females using RIVELSA may experience unscheduled (breakthrough or intracyclic) bleeding and spotting, especially during the first 3 months of use. Bleeding irregularities may resolve over time or by changing to a different contraceptive product. If unscheduled bleeding persists or occurs after previously regular cycles on RIVELSA, evaluate for causes such as pregnancy or malignancy.

When prescribing RIVELSA, consider the occurrence of fewer scheduled menses (4 per year instead of 13 per year) against the occurrence of increased unscheduled bleeding and/or spotting. A 12-month open-label study of the efficacy of RIVELSA in preventing pregnancy assessed scheduled and unscheduled bleeding [see Clinical Studies (14)] in 3,597 women who completed 34,087 28-day cycles of exposure. A total of 178 (4.9%) of the women discontinued RIVELSA, at least in part, due to bleeding and/or spotting.

Scheduled (withdrawal) bleeding and/or spotting remained fairly stable over time, with an average of 3 to 4 days of bleeding and/or spotting per each 91-day cycle. Unscheduled bleeding and unscheduled spotting decreased over successive 91-day cycles. Table 2 below presents the number of days with unscheduled bleeding, spotting, and unscheduled bleeding and/or spotting in Treatment Cycles 1 to 4.

Table 2: Number of Unscheduled Bleeding, Spotting and Bleeding and/or Spotting Days per 91-day Cycle

Cycle (N) | Days of Unscheduled Bleeding per 84-Day Interval |  |  |  | Median Days Per Subject-Month
Cycle (N) | Mean | Q1 | Median | Q3 | Median Days Per Subject-Month
1 (3330) | 7.2 | 0 | 4 | 10 | 1.0
2 (2820) | 3.3 | 0 | 0 | 4 | 0.0
3 (2433) | 2.5 | 0 | 0 | 3 | 0.0
4 (2213) | 2.2 | 0 | 0 | 2 | 0.0
Cycle; (N) | Days of Unscheduled Spotting per 84-Day Interval |  |  |  | Median Days Per Subject-Month
Cycle; (N) | Mean | Q1 | Median | Q3 | Median Days Per Subject-Month
1 (3330) | 10.7 | 2 | 7 | 15 | 1.8
2 (2820) | 6.7 | 0 | 3 | 9 | 0.8
3 (2433) | 5.2 | 0 | 2 | 6 | 0.5
4 (2213) | 4.4 | 0 | 1 | 5 | 0.3
Cycle; (N) | Days of Unscheduled Bleeding and/or Spotting per 84-Day Interval |  |  |  | Median Days Per Subject-Month
Cycle; (N) | Mean | Q1 | Median | Q3 | Median Days Per Subject-Month
1 (3330) | 17.9 | 5 | 14 | 27 | 3.5
2 (2820) | 10.0 | 1 | 5 | 14 | 1.3
3 (2433) | 7.7 | 0 | 3 | 10 | 0.8
4 (2213) | 6.6 | 0 | 3 | 8 | 0.8

Q1=Quartile 1: 25% of women had ≤ this number of days of unscheduled bleeding/spotting

Median: 50% of women had ≤ this number of days of unscheduled bleeding/spotting

Q3=Quartile 3: 75% of women had ≤ this number of days of unscheduled bleeding/spotting

Figure 2 shows the percent of RIVELSA subjects in the primary clinical trial with ≥7 days or ≥20 days of unscheduled bleeding and/or spotting, or just unscheduled bleeding, during each 91-day treatment cycle.

Figure 2: Percent of Women Taking RIVELSA Who Reported Unscheduled Bleeding and/or Spotting

If unscheduled spotting or bleeding occurs, instruct the patient to continue on the same regimen. If the bleeding is persistent or prolonged, advise the patient to consult her healthcare provider.

Amenorrhea and Oligomenorrhea

Females who use RIVELSA may experience absence of scheduled (withdrawal) bleeding, even if they are not pregnant. Based on data from the clinical trial, amenorrhea occurred in approximately 1.9% of women during Cycle 1, 7.7% during Cycle 2, 10.7% during Cycle 3, and 10.1% during Cycle 4 using RIVELSA.

Rule out pregnancy in the event of amenorrhea. Some women may experience amenorrhea or oligomenorrhea after stopping RIVELSA, especially if these conditions were pre-existent.

5.10 Depression

Carefully observe females with a history of depression and discontinue RIVELSA if depression recurs to a serious degree. Six cases of suicidality (suicide attempts and suicidal behavior) were reported in the clinical trial; several of these cases occurred in women with a psychiatric history.

Data on the association of COCs with onset of depression or exacerbation of existing depression are limited.

5.11 Malignant Neoplasms

Breast Cancer

RIVELSA is contraindicated in females who currently have or have had breast cancer because breast cancer may be hormonally sensitive [see Contraindications (4)].

Epidemiology studies have not found a consistent association between use of combined oral contraceptives (COCs) and breast cancer risk. Studies do not show an association between ever (current or past) use of COCs and risk of breast cancer. However, some studies report a small increase in the risk of breast cancer among current or recent users (<6 months since last use) and current users with longer duration of COC use [see Postmarketing Experience (6.2)].

Cervical Cancer

Some studies suggest that COCs are associated with an increase in the risk of cervical cancer or intraepithelial neoplasia. However, there is controversy about the extent to which these findings are due to differences in sexual behavior and other factors.

5.12 Effect on Binding Globulins

The estrogen component of RIVELSA may raise the serum concentrations of thyroxine-binding globulin, sex hormone-binding globulin and cortisol-binding globulin. The dose of replacement thyroid hormone or cortisol therapy may need to be increased.

5.13 Hereditary Angioedema

In women with hereditary angioedema, exogenous estrogens, including RIVELSA, may induce or exacerbate symptoms of hereditary angioedema.

5.14 Chloasma

Chloasma may occur with RIVELSA use, especially in females with a history of chloasma gravidarum. Advise females with a history of chloasma to avoid exposure to the sun or ultraviolet radiation while taking RIVELSA.

6 ADVERSE REACTIONS

The following serious adverse reactions with the use of COCs are discussed elsewhere in the labeling:

- Serious cardiovascular events [see Boxed Warning and Warnings and Precautions (5.1)]
- Vascular events [see Warnings and Precautions (5.1)]
- Liver disease [see Warnings and Precautions (5.2)]

6.1 Clinical Trial Experience

Because clinical trials are conducted under widely varying conditions, adverse reaction rates observed in the clinical trials of a drug cannot be directly compared to the rates in the clinical trials of another drug and may not reflect the rates observed in practice.

The safety data described below are from a 12-month, US, open-label study, which enrolled women aged 18-40, of whom 3,597 took at least one dose of RIVELSA (2,661 woman-years of exposure) [see Clinical Studies (14)].

Adverse Reactions Leading to Study Discontinuation: 13.3% of the women discontinued from the clinical trial due to an adverse reaction; the most common adverse reactions (≥1% of women) leading to discontinuation were heavy/irregular bleeding (5.0%), mood swings/alteration/affect lability (1.4%), headaches/migraines (1.3%), weight increased (1.3%) and acne (1.0%).

Common Adverse Reactions (≥2% of women): headaches (12.2%), heavy/irregular vaginal bleeding (9.7%), nausea/vomiting (8.8%), acne (5.4%), dysmenorrhea (5.4%), weight increased (4.6%), mood changes (depression, depressed mood, crying, major depression, affective disorder, depression suicidal, dysthymic disorder) (2.9%), anxiety/panic attack (2.4%), breast tenderness/pain/discomfort (2.2%), migraine (2.0%).

Serious Adverse Reactions (≥2 women): abortion spontaneous, suicide attempt, cholecystitis/cholelithiasis, deep vein thrombosis, ectopic pregnancy.

6.2 Postmarketing Experience

Five studies that compared breast cancer risk between ever-users (current or past use) of COCs and never-users of COCs reported no association between ever use of COCs and breast cancer risk, with effect estimates ranging from 0.90 - 1.12 (Figure 3).

Three studies compared breast cancer risk between current or recent COC users (<6 months since last use) and never users of COCs (Figure 2). One of these studies reported no association between breast cancer risk and COC use. The other two studies found an increased relative risk of 1.19 - 1.33 with current or recent use. Both of these studies found an increased risk of breast cancer with current use of longer duration, with relative risks ranging from 1.03 with less than one year of COC use to approximately 1.4 with more than 8-10 years of COC use.

Figure 3: Relevant Studies of Risk of Breast Cancer with Combined Oral Contraceptives

RR = relative risk; OR = odds ratio; HR = hazard ratio. “ever COC” are females with current or past COC use; “never COC use” are females that never used COCs.

The following adverse reactions have been identified during post-approval use of extended-cycle COCs containing levonorgestrel and ethinyl estradiol. Because these reactions are reported voluntarily from a population of uncertain size, it is not always possible to reliably estimate their frequency or establish a causal relationship to drug exposure.

Gastrointestinal disorders: abdominal distension, vomiting

General disorders and administration site conditions: chest pain, fatigue, malaise, edema peripheral, pain

Immune system disorders: hypersensitivity reaction

Investigations: blood pressure increased

Musculoskeletal and connective tissue disorders: muscle spasms, pain in extremity

Nervous system disorders: dizziness, loss of consciousness

Psychiatric disorders: insomnia

Reproductive and breast disorders: dysmenorrhea

Respiratory, thoracic and mediastinal disorders: pulmonary embolism, pulmonary thrombosis

Skin and subcutaneous tissue disorders: alopecia

Vascular disorders: thrombosis

7 DRUG INTERACTIONS

The sections below provide information on substances for which data on drug interactions with COCs are available. There is little information available about the clinical effect of most drug interactions that may affect COCs. However, based on the known pharmacokinetic effects of these drugs, clinical strategies to minimize any potential adverse effect on contraceptive effectiveness or safety are suggested.

Consult the approved product labeling of all concurrently used drugs to obtain further information about interactions with COCs or the potential for metabolic enzyme or transporter system alterations.

No drug-drug interaction studies were conducted with RIVELSA.

7.1 Effects of Other Drugs on Combined Oral Contraceptives

Substances Decreasing the Plasma Concentrations of COCs and Potentially Diminishing the Efficacy of COCs:

Table 3 includes substances that demonstrated an important drug interaction with RIVELSA.

Table 3: Significant Drug Interactions Involving Substances That Affect COCs

Metabolic Enzyme Inducers
Clinical effect | - Concomitant use of COCs with metabolic enzyme inducers may decrease the plasma concentrations of the estrogen and/or progestin component of COCs. - Decreased exposure of the estrogen and/or progestin component of COCs may potentially diminish the effectiveness of COCs and may lead to contraceptive failure or an increase in breakthrough bleeding.
Prevention or management | - Counsel females to use an alternative method of contraception or a backup method when enzyme inducers are used with COCs. - Continue backup contraception for 28 days after discontinuing the enzyme inducer to maintain contraceptive reliability.
Examples | Aprepitant, barbiturates, bosentan, carbamazepine, efavirenz, felbamate, griseofulvin, oxcarbazepine, phenytoin, rifampin, rifabutin, rufinamide, topiramate, products containing St. John’s worta, and certain protease inhibitors (see separate section on protease inhibitors below).
Colesevelam
Clinical effect | - Concomitant use of COCs with colesevelam significantly decreases systemic exposure of ethinyl estradiol. - Decreased exposure of the estrogen component of COCs may potentially reduce contraceptive efficacy or result in an increase in breakthrough bleeding, depending on the strength of ethinyl estradiol in the COC.
Prevention or management | Administer 4 or more hours apart to attenuate this drug interaction.

a Induction potency of St. John’s wort may vary widely based on preparation.

Substances increasing the systemic exposure of COCs:

Co-administration of atorvastatin or rosuvastatin and COCs containing ethinyl estradiol increase systemic exposure of ethinyl estradiol by approximately 20 to 25 percent. Ascorbic acid and acetaminophen may increase systemic exposure of ethinyl estradiol, possibly by inhibition of conjugation. CYP3A4 inhibitors such as itraconazole, voriconazole, fluconazole, grapefruit juice, or ketoconazole may increase systemic exposure of the estrogen and/or progestin component of COCs.

Human immunodeficiency virus (HIV)/hepatitis C virus (HCV) protease inhibitors and non-nucleoside reverse transcriptase inhibitors:

Significant decreases in systemic exposure of the estrogen and/or progestin have been noted when COCs are co-administered with some HIV protease inhibitors (e.g., nelfinavir, ritonavir, darunavir/ritonavir, (fos)amprenavir/ritonavir, lopinavir/ritonavir, and tipranavir/ritonavir), some HCV protease inhibitors (e.g., boceprevir and telaprevir), and some non-nucleoside reverse transcriptase inhibitors (e.g., nevirapine).

In contrast, significant increases in systemic exposure of the estrogen and/or progestin have been noted when COCs are co-administered with certain other HIV protease inhibitors (e.g., indinavir and atazanavir/ritonavir) and with other non-nucleoside reverse transcriptase inhibitors (e.g., etravirine).

7.2 Effects of Combined Oral Contraceptives on Other Drugs

Table 4 provides significant drug interaction information for drugs co-administered with RIVELSA.

Table 4: Significant Drug Interaction Information for Drugs Co-Administered With COCs

Lamotrigine
Clinical effect | - Concomitant use of COCs with lamotrigine may significantly decrease systemic exposure of lamotrigine due to induction of lamotrigine glucuronidation. - Decreased systemic exposure of lamotrigine may reduce seizure control.
Prevention or management | Dose adjustment may be necessary. Consult the approved product labeling for lamotrigine.
Thyroid Hormone Replacement Therapy or Corticosteroid Replacement Therapy
Clinical effect | Concomitant use of COCs with thyroid hormone replacement therapy or corticosteroid replacement therapy may increase systemic exposure of thyroid-binding and cortisol-binding globulin [see Warnings and Precautions (5.12)].
Prevention or management | The dose of replacement thyroid hormone or cortisol therapy may need to be increased. Consult the approved product labeling for the therapy in use [see Warnings and Precautions (5.12)].
Other Drugs
Clinical effect | Concomitant use of COCs may decrease systemic exposure of acetaminophen, morphine, salicylic acid, and temazepam. Concomitant use with ethinyl estradiol-containing COCs may increase systemic exposure of other drugs (e.g., cyclosporine, prednisolone, theophylline, tizanidine, and voriconazole).
Prevention or management | The dosage of drugs that can be affected by this interaction may need to be increased. Consult the approved product labeling for the concomitantly used drug.

7.3 Concomitant Use with Hepatitis C Virus (HCV) Combination Therapy – Liver Enzyme Elevation

Do not co-administer RIVELSA with HCV drug combinations containing ombitasvir/paritaprevir/ritonavir, with or without dasabuvir [see Warnings and Precautions (5.4)], and glecaprevir/pibrentasvir due to potential for ALT elevations.

7.4 Effect on Laboratory Tests

The use of COCs may influence the results of certain laboratory tests, such as coagulation factors, lipids, glucose tolerance, and binding proteins.

8 USE IN SPECIFIC POPULATIONS

8.1 Pregnancy

Risk Summary

There is no use for contraception in pregnancy; therefore, RIVELSA should be discontinued during pregnancy. Epidemiologic studies and meta-analyses have not found an increased risk of genital or non-genital birth defects (including cardiac anomalies and limb-reduction defects) following exposure to CHCs before conception or during early pregnancy.

In the U.S. general population, the estimated background risk of major birth defects and miscarriage in clinically recognized pregnancies is 2 to 4 percent and 15 to 20 percent, respectively.

8.2 Lactation

Risk Summary

Contraceptive hormones and/or metabolites are present in human milk. CHCs can reduce milk production in breastfeeding females. This reduction can occur at any time but is less likely to occur once breastfeeding is well-established. When possible, advise the nursing female to use other methods of contraception until she discontinues breastfeeding [See Dosage and Administration (2.1)].The developmental and health benefits of breastfeeding should be considered along with the mother’s clinical need for RIVELSA and any potential adverse effects on the breastfed child from RIVELSA or the underlying maternal condition.

8.4 Pediatric Use

Safety and efficacy of RIVELSA have been established in women of reproductive age. Efficacy is expected to be the same for postpubertal adolescents under the age of 18 as for users 18 years and older. Use of RIVELSA before menarche is not indicated.

8.6 Hepatic Impairment

No studies have been conducted to evaluate the effect of hepatic impairment on the disposition of RIVELSA. However, steroid hormones may be poorly metabolized in patients with hepatic impairment. RIVELSA is contraindicated in females with acute hepatitis or severe decompensated cirrhosis. [See Contraindications (4) and Warnings and Precautions (5.2)]

10 OVERDOSAGE

There have been no reports of serious ill effects from overdose of oral contraceptives, including ingestion by children. Overdosage may cause withdrawal bleeding in females and nausea.

11 DESCRIPTION

RIVELSA (levonorgestrel/ethinyl estradiol and ethinyl estradiol) tablets is an extended-cycle oral contraceptive. RIVELSA consists of 42 light pink tablets containing 0.15 mg levonorgestrel and 0.02 mg ethinyl estradiol, 21 pink tablets containing 0.15 mg levonorgestrel and 0.025 mg ethinyl estradiol, and 21 purple tablets containing 0.15 mg levonorgestrel and 0.03 mg ethinyl estradiol, and 7 yellow tablets containing 0.01 mg ethinyl estradiol. Levonorgestrel is a progestin and ethinyl estradiol is an estrogen.

The structural formulas, molecular formulas, molecular weights, and chemical names for the active components are shown below:

Levonorgestrel

C21H28O2 MW: 312.4

Levonorgestrel is chemically 18,19-Dinorpregn-4-en-20-yn-3-one, 13-ethyl-17-hydroxy-(17α)-(-)-.

Ethinyl Estradiol

C20H24O2 MW: 296.4

Ethinyl Estradiol is 19-Norpregna-1,3,5(10)-trien-20-yne-3,17-diol, (17α)-.

Each light pink tablet contains the following inactive ingredients:

anhydrous lactose, D&C Red no. 27/phloxine aluminum lake, FD&C Blue no. 2/Indigo Carmine aluminum lake, FD&C Yellow no. 6/Sunset Yellow FCF aluminum lake, hypromellose, lactose monohydrate, microcrystalline cellulose, magnesium stearate, polyethylene glycol/macrogol, titanium dioxide, and triacetin.

Each pink tablet contains the following inactive ingredients:

anhydrous lactose, D&C Red no. 27/phloxine aluminum lake, FD&C Blue no. 2/Indigo Carmine aluminum lake, hypromellose, lactose monohydrate, microcrystalline cellulose, magnesium stearate, polyethylene glycol/macrogol, titanium dioxide and triacetin.

Each purple tablet contains the following inactive ingredients:

anhydrous lactose, D&C Red no. 27/phloxine aluminum lake, FD&C Blue no. 1/Brilliant Blue FCF aluminum lake, hypromellose, lactose monohydrate, microcrystalline cellulose, magnesium stearate, polyethylene glycol/macrogol, titanium dioxide and triacetin.

Each yellow tablet contains the following inactive ingredients:

anhydrous lactose, D&C Yellow no. 10 aluminum lake, FD&C Yellow no. 6/Sunset Yellow FCF aluminum lake, hypromellose, magnesium stearate, microcrystalline cellulose, polacrilin potassium, polyethylene glycol/macrogol, polysorbate 80 and titanium dioxide.

12 CLINICAL PHARMACOLOGY

12.1 Mechanism of Action

CHCs prevent pregnancy primarily by suppressing ovulation.

12.2 Pharmacodynamics

No pharmacodynamic studies were conducted with RIVELSA.

12.3 Pharmacokinetics

Absorption

Ethinyl estradiol and levonorgestrel are absorbed with maximum plasma concentrations occurring within 2 hours after RIVELSA administration. Levonorgestrel is completely absorbed after oral administration (bioavailability nearly 100%) and is not subject to first-pass metabolism. Ethinyl estradiol is absorbed from the gastrointestinal tract but, due to first-pass metabolism in gut mucosa and liver, the bioavailability of ethinyl estradiol is approximately 40%. The effect of food on the rate and the extent of levonorgestrel and ethinyl estradiol absorption following oral administration of RIVELSA has not been evaluated.

The mean plasma pharmacokinetic parameters of levonorgestrel following administration of another levonorgestrel/ethinyl estradiol combination tablet with an equal dose of levonorgestrel for 84 days, in healthy women are reported in Table 5.

Table 5: Mean Pharmacokinetic Parameters for 150 mcg Levonorgestrel Following Administration of a Levonorgestrel/Ethinyl Estradiol Combination Tablet Once Daily for 84 Days

 | AUC0-24 hr; (mean ± SD) | Cmax; (mean ± SD) | Tmax; (mean ± SD)
Day 1 | 18.2 ± 6.1 ng•hr/mL | 3.0 ± 1.0 ng/mL | 1.3 ± 0.4 hours
Day 21 | 64.4 ± 25.1 ng•hr/mL | 6.2 ± 1.6 ng/mL | 1.3 ± 0.4 hours
Day 84 | 60.2 ± 24.6 ng•hr/mL | 5.5 ± 1.6 ng/mL | 1.3 ± 0.3 hours

Following repeated daily dosing of levonorgestrel/ethinyl estradiol oral contraceptives, levonorgestrel plasma concentrations accumulate more than predicted based on single-dose pharmacokinetics, due in part, to increased sex hormone binding globulin (SHBG) levels that are induced by ethinyl estradiol, and a possible reduction in hepatic metabolic capacity.

Systemic exposure to ethinyl estradiol following administration of a levonorgestrel/ethinyl estradiol combination tablet increases linearly in an approximate dose-proportional manner over the range of doses of 20 mcg to 30 mcg within this product. Systemic exposure to ethinyl estradiol (as assessed by AUC) at steady state following administration of levonorgestrel/ethinyl estradiol oral contraceptives is approximately 20% higher than expected based on single-dose data for the dose range of 20-30 mcg.

Distribution

The apparent volume of distribution of levonorgestrel is reported to be approximately 1.8 L/kg. Levonorgestrel is about 97.5 - 99% protein-bound, principally to SHBG and, to a lesser extent, serum albumin.

The apparent volume of distribution of ethinyl estradiol is reported to be approximately 4.3 L/kg. Ethinyl estradiol is about 95-97% bound to serum albumin. Ethinyl estradiol does not bind to SHBG, but induces SHBG synthesis, which leads to decreased levonorgestrel clearance.

Metabolism

Following absorption, levonorgestrel is conjugated at the 17β-OH position to form sulfate and to a lesser extent, glucuronide conjugates in plasma. Significant amounts of conjugated and unconjugated 3α,5β-tetrahydrolevonorgestrel are also present in plasma, along with much smaller amounts of 3α,5α-tetrahydrolevonorgestrel and 16β-hydroxylevonorgestrel. Levonorgestrel and its phase I metabolites are excreted primarily as glucuronide conjugates. Metabolic clearance rates may differ among individuals by several-fold, and this may account in part for the wide variation observed in levonorgestrel concentrations among users.

First-pass metabolism of ethinyl estradiol involves formation of ethinyl estradiol-3-sulfate in the gut wall, followed by 2-hydroxylation of a portion of the remaining untransformed ethinyl estradiol by hepatic cytochrome P-450 3A4 (CYP3A4). Levels of CYP3A4 vary widely among individuals and can explain the variation in rates of ethinyl estradiol hydroxylation. Hydroxylation at the 4-, 6-, and 16- positions may also occur, although to a much lesser extent than 2-hydroxylation. The various hydroxylated metabolites are subject to further methylation and/or conjugation.

Excretion

About 45% of levonorgestrel and its metabolites are excreted in the urine and about 32% are excreted in feces, mostly as glucuronide conjugates. The mean terminal elimination half-life for levonorgestrel after a single dose of RIVELSA ranged from 36-41 hours.

Ethinyl estradiol is excreted in the urine and feces as glucuronide and sulfate conjugates, and it undergoes enterohepatic recirculation. The terminal elimination half-life of ethinyl estradiol following single doses of RIVELSA is approximately 16.5 hours.

13 NONCLINICAL TOXICOLOGY

13.1 Carcinogenesis, Mutagenesis, Impairment of Fertility

[See Warnings and Precautions (5.2, 5.11)].

14 CLINICAL STUDIES

In a 12-month, multicenter, open-label, single-arm clinical trial conducted in the US, 3,667 women, 18-40 years old, were enrolled and 3,565 were treated for up to four 91-day cycles, which equates to thirteen 28-day cycles, to assess the safety and efficacy of RIVELSA, completing the equivalent of 33,895 28-day cycles of exposure. The racial demographic of those treated was: Caucasian (64%), African-American (19%), Hispanic (11%), Asian (2%), and Other (3%). There were no exclusions for body mass index (BMI) or weight. The weight range of those women treated was 83 to 402 lbs., with a mean weight of 162.5 lbs. Among the women in the trial, 44% were current hormonal contraceptive users, 39% were prior users (who had used hormonal contraceptives in the past), and 17% were new starters. Of treated women, 13.2% were lost to follow-up, 12.8% discontinued due to an adverse event, and 6.1% discontinued by withdrawing their consent.

The pregnancy rate (Pearl Index [PI]) in women aged 18-35 years was 3.19 pregnancies per 100 woman-years of use (95% confidence interval 2.49, 4.03), based on 70 pregnancies that occurred after the onset of treatment and up to and including 7 days after the last pill. Cycles in which conception did not occur, but which included the use of backup contraception, were not included in the calculation of the PI. The PI includes patients who did not take the drug correctly.

16 HOW SUPPLIED/STORAGE AND HANDLING

How Supplied

RIVELSA (levonorgestrel/ethinyl estradiol and ethinyl estradiol) tablets are available as round, film-coated, unscored, biconvex tablets debossed with TV on one side, packaged in an Extended-Cycle Tablet Dispenser, each containing a 13-week supply of the tablets in the following order:

- 42 light pink tablets, each containing 0.15 mg of levonorgestrel and 0.02 mg ethinyl estradiol: debossed with 076 on the other side
- 21 pink tablets containing 0.15 mg of levonorgestrel and 0.025 mg ethinyl estradiol: debossed with 075 on the other side
- 21 purple tablets containing 0.15 mg of levonorgestrel and 0.03 mg ethinyl estradiol: debossed with 074 on the other side and
- 7 yellow tablets containing 0.01 mg of ethinyl estradiol: debossed with 077 on the other side

Box of 2 Extended-Cycle Tablet Dispensers NDC 0093-6031-82

Storage and Handling

Store at 20°C to 25°C (68°F to 77°F) [See USP Controlled Room Temperature].

17 PATIENT COUNSELING INFORMATION

Advise the patient to read the FDA-approved patient labeling (Patient Information and Instructions for Use).

Counsel patients about the following information:

Cigarette Smoking

Cigarette smoking increases the risk of serious cardiovascular events from COC use, Women who are over 35 years old and smoke should not use RIVELSA [see Boxed Warning and Warnings and Precautions (5.1)].

Venous Thromboembolism

Increased risk of VTE compared to non-users of COCs is greatest after initially starting a COC or restarting (following a 4-week or greater pill-free interval) the same or a different COC [see Warnings and Precautions (5.1)].

Use during Pregnancy

Instruct females to stop RIVELSA if pregnancy is confirmed during treatment.

Sexually Transmitted Infections

RIVELSA does not protect against HIV infection and other sexually transmitted infections.

Dosing and Missed Pill Instructions

Patients should take one tablet daily by mouth at the same time every day. Instruct patients what to do in the event pills are missed. See [see Dosage and Administration (2.3)]. Instruct patients to see, “What to do if you miss pills” section of the FDA-Approved Instructions for Use.

Need for Additional Contraception

Postpartum females who have not yet had a period when they start RIVELSA need to use an additional method of contraception until they have taken a light pink tablet for 7 consecutive days [see Dosage and Administration (2.2)].

There is a need for a backup or alternative method of contraception when enzyme inducers are used with RIVELSA [see Drug Interactions (7.1)].

Lactation

RIVELSA may reduce breast milk production. This is less likely to occur if breastfeeding is well established. When possible, nursing women should use other methods of contraception until they have discontinued breastfeeding [see Use in Specific Populations (8.2)].

Amenorrhea and Possible Symptoms of Pregnancy

Amenorrhea may occur [see Warnings and Precautions (5.9)]. Advise the patient to contact a healthcare provider in the event of amenorrhea with symptoms of pregnancy, such as morning sickness or unusual breast tenderness [see Use in Specific Populations (8.1].

Depression

Depressed mood and depression may occur. Women should contact their healthcare provider if mood changes and depressive symptoms occur, including shortly after initiating the treatment [see Warnings and Precautions (5.10)].

Manufactured for:
Teva Pharmaceuticals
Parsippany, NJ 07054

Rev. 10/2024

RIV-005

©2024 Teva Pharmaceuticals, Inc.

FDA-approved Patient Labeling

PATIENT INFORMATION

RIVELSA®

(levonorgestrel/ethinyl estradiol and ethinyl estradiol tablets)

What is the most important information I should know about RIVELSA?

Do not use RIVELSA if you smoke cigarettes and are over 35 years old. Smoking increases your risk of serious cardiovascular side effects from birth control pills, including death from heart attack, blood clots or stroke. This risk increases with age and the number of cigarettes you smoke.

What is RIVELSA?

RIVELSA is a birth control pill (hormonal contraceptive) used by women to prevent pregnancy. It contains two female hormones, an estrogen called ethinyl estradiol, and a progestin called levonorgestrel.

How does RIVELSA work for contraception?

Your chance of getting pregnant depends on how well you follow the directions for taking your birth control pills. The more carefully you follow the directions, the less chance you have of getting pregnant.

Based on the results of a single clinical study lasting 12 months, 2 to 4 women out of 100 women may get pregnant during the first year they use RIVELSA.

The following chart shows the chance of getting pregnant for women who use different methods of birth control. Each box on the chart contains a list of birth control methods that are similar in effectiveness. The most effective methods are at the top of the chart. The box on the bottom of the chart shows the chance of getting pregnant for women who do not use birth control and are trying to get pregnant.

Who should not take RIVELSA?

Do not take RIVELSA if you:

- smoke and are over 35 years of age
- had blood clots in your arms, legs, eyes, or lungs
- have certain heart valve problems or heart rhythm abnormalities that can cause blood clots to form in the heart
- had a stroke
- had a heart attack
- have an inherited problem with your blood that makes it clot more than normal
- have liver disease, including liver tumors
- have high blood pressure that medicine can't control
- take any Hepatitis C drug combination containing ombitasvir/paritaprevir/ritonavir, with or without dasabuvir. This may increase levels of the liver enzyme “alanine aminotransferase” (ALT) in the blood
- have diabetes with kidney, eye, nerve, or blood vessel damage
- have certain kinds of severe migraine headaches with aura, numbness, weakness or changes in vision, or have any migraine headaches if you are over age 35
- have any unexplained bleeding from the vagina
- had breast cancer which may be sensitive to female hormones

If any of these conditions happens to you while you are taking RIVELSA, stop taking RIVELSA right away and talk to your healthcare provider. Use non-hormonal contraception (such as condoms and spermicide) when you stop taking RIVELSA.

What should I tell my healthcare provider before taking RIVELSA?

Tell your healthcare provider if you:

- are pregnant or think you may be pregnant
- are depressed now or have been depressed in the past
- had yellowing of your skin or eyes (jaundice) caused by pregnancy (cholestasis of pregnancy)
- are breastfeeding or plan to breastfeed. RIVELSA may decrease the amount of breast milk you make. A small amount of the hormones in RIVELSA may pass into your breast milk. Talk to your healthcare provider about the best birth control method for you while breastfeeding.

Tell your healthcare provider if you have ever had any of the conditions listed in, “Who should not take RIVELSA” above. Your healthcare provider may recommend another method of birth control.

Tell your healthcare provider about all the medicines you take, including prescription and over-the-counter medicines, vitamins and herbal supplements.

RIVELSA may affect the way other medicines work, and other medicines may affect how well RIVELSA works.

Know the medicines you take. Keep a list of them to show your healthcare provider and pharmacist when you get a new medicine.

How should I take RIVELSA?

Read the Instructions for Use at the end of this Patient Information.

What are the most serious risks of taking birth control pills?

Like pregnancy, birth control pills increase the risk of serious blood clots, especially in women who have other risk factors, such as smoking, obesity, or age greater than 35. This increased risk is highest when you first start taking birth control pills and when you restart the same or different birth control pills after not using them for a month or more.

It is possible to die from a problem caused by a blood clot, such as a heart attack or a stroke. Some examples of serious blood clots are blood clots in the:

- Legs (deep vein thrombosis)
- Lungs (pulmonary embolus)
- Eyes (loss of eyesight)
- Heart (heart attack)
- Brain (stroke)

Women who take birth control pills may get:

- High blood pressure
- Gallbladder problems
- Rare cancerous or noncancerous liver tumors

All of these events are uncommon in healthy women.

Call your healthcare provider right away if you have:

- Persistent leg pain
- Sudden shortness of breath
- Sudden blindness, partial or complete
- Severe pain or pressure in your chest
- Sudden, severe headache unlike your usual headaches
- Weakness or numbness in an arm or leg, or trouble speaking
- Yellowing of the skin or eyeballs

What are common side effects of birth control pills?

The most common side effects of birth control pills are:

- Spotting or bleeding between menstrual periods
- Nausea
- Breast tenderness
- Headache

These side effects are usually mild and usually disappear with time.

Less common side effects are:

- Acne
- Less sexual desire
- Bloating or fluid retention
- Blotchy darkening of the skin, especially on the face
- High blood sugar, especially in women who already have diabetes
- High fat (cholesterol, triglyceride) levels in the blood
- Depression, especially if you have had depression in the past. Call your healthcare provider immediately if you have any thoughts of harming yourself.
- Problems tolerating contact lenses
- Weight gain

This is not a complete list of possible side effects. Talk to your healthcare provider if you develop any side effects that concern you. You may report side effects to the FDA at 1‑800-FDA-1088.

No serious problems have been reported from a birth control pill overdose, even when accidentally taken by children.

What else should I know about taking RIVELSA?

Birth control pills do not protect you against any sexually transmitted infection, including HIV, the virus that causes AIDS.

Do not skip any pills, even if you do not have sex often.

Birth control pills should not be taken during pregnancy. However, birth control pills taken by accident during pregnancy are not known to cause birth defects.

You should stop RIVELSA at least four weeks before you have major surgery and not restart it for at least two weeks after the surgery, due to an increased risk of blood clots.

If you are breastfeeding, consider another birth control method until you are ready to stop breastfeeding. Birth control pills that contain estrogen, like RIVELSA, may decrease the amount of milk you make. A small amount of the pill's hormones pass into breast milk.

Tell your healthcare provider about all medicines and herbal products that you take. Some medicines and herbal products may make birth control pills less effective, including:

- barbiturates
- bosentan
- carbamazepine
- felbamate
- griseofulvin
- oxcarbazepine
- phenytoin
- rifampin
- St. John’s wort
- topiramate

Use a backup or alternative birth control method when you take medicines that may make birth control pills less effective.

If you have vomiting or diarrhea, your birth control pills may not work as well. Use another birth control method, like condoms and spermicide, until you check with your healthcare provider.

Birth control pills may interact with lamotrigine, an anticonvulsant used for epilepsy. This may increase the risk of seizures, so your healthcare provider may need to adjust the dose of lamotrigine.

Women on thyroid hormone replacement therapy may need increased doses of thyroid hormone.

How should I store RIVELSA?

- Store RIVELSA at room temperature between 68°F to 77°F (20°C to 25°C).
- Keep RIVELSA and all medicines out of the reach of children.

General information about RIVELSA

Medicines are sometimes prescribed for purposes other than those listed in a Patient Information leaflet. Do not use RIVELSA for a condition for which it was not prescribed. Do not give RIVELSA to anyone else.

If you have concerns or questions, ask your healthcare provider. You may also ask your healthcare provider for a more detailed label written for medical professionals.

Do birth control pills cause cancer?

It is not known if hormonal birth control pills cause breast cancer. Some studies, but not all, suggest that there could be a slight increase in the risk of breast cancer among current users with longer duration of use.

If you have breast cancer now, or have had it in the past, do not use hormonal birth control because some breast cancers are sensitive to hormones.

Women who use birth control pills may have a slightly higher chance of getting cervical cancer. However, this may be due to other reasons such as having more sexual partners.

What if I want to become pregnant?

You may stop taking the pill whenever you wish. Consider a visit with your healthcare provider for a pre-pregnancy checkup before you stop taking the pill.

What should I know about my period when taking RIVELSA?

When you take RIVELSA, which has a 91-day extended dosing cycle, you should expect to have 4 scheduled periods per year (bleeding when you are taking the 7 yellow pills). Each period is likely to last about 3-4 days. However, you will probably have more bleeding or spotting between your scheduled periods than if you were using a birth control pill with a 28-day dosing cycle. This bleeding or spotting tends to decrease with each additional cycle. Do not stop taking RIVELSA because of this bleeding or spotting. If the spotting continues for more than 7 consecutive days or if the bleeding is heavy, call your healthcare provider.

What if I miss my scheduled period when taking RIVELSA?

You should consider the possibility that you are pregnant if you miss your scheduled period (no bleeding on the days that you are taking yellow pills). Because scheduled periods are less frequent when you are taking RIVELSA, notify your healthcare provider that you have missed your period and that you are taking RIVELSA. Also notify your healthcare provider if you have symptoms of pregnancy such as morning sickness or unusual breast tenderness. It is important that your healthcare provider evaluates you to determine if you are pregnant. Stop taking RIVELSA if it is determined that you are pregnant.

What are the ingredients in RIVELSA?

Active ingredients:

Light pink tablets, pink tablets, purple tablets: levonorgestrel acetate and ethinyl estradiol

Yellow tablets: ethinyl estradiol

Inactive ingredients:

Light pink tablets: anhydrous lactose, D&C Red no. 27/phloxine aluminum lake, FD&C Blue no. 2/Indigo Carmine aluminum lake, FD&C Yellow no. 6/Sunset Yellow FCF aluminum lake, hypromellose, lactose monohydrate, microcrystalline cellulose, magnesium stearate, polyethylene glycol/macrogol, titanium dioxide, and triacetin.

Pink tablets: anhydrous lactose, D&C Red no. 27/phloxine aluminum lake, FD&C Blue no. 2/Indigo Carmine aluminum lake, hypromellose, lactose monohydrate, microcrystalline cellulose, magnesium stearate, polyethylene glycol/macrogol, titanium dioxide and triacetin.

Purple tablets: anhydrous lactose, D&C Red no. 27/phloxine aluminum lake, FD&C Blue no. 1/Brilliant Blue FCF aluminum lake, hypromellose, lactose monohydrate, microcrystalline cellulose, magnesium stearate, polyethylene glycol/macrogol, titanium dioxide and triacetin.

Yellow tablets: anhydrous lactose, D&C Yellow no. 10 aluminum lake, FD&C Yellow no. 6/Sunset Yellow FCF aluminum lake, hypromellose, magnesium stearate, microcrystalline cellulose, polacrilin potassium, polyethylene glycol/macrogol, polysorbate 80 and titanium dioxide.

INSTRUCTIONS FOR USE

RIVELSA®

(levonorgestrel/ethinyl estradiol and ethinyl estradiol tablets)

Important information about taking RIVELSA

1. Take one pill every day at the same time. Take pills in the order directed on the Extended-Cycle Tablet Dispenser.
2. Do not skip pills or delay taking your pills. If you miss pills (including starting the pack late), you could get pregnant. The more pills you miss, the more likely you are to get pregnant.
3. You may have spotting or light bleeding or feel sick to your stomach during the first few months of taking RIVELSA. If you feel sick to your stomach, do not stop taking the pill. The problem will usually go away. If it doesn't go away, check with your healthcare provider.
4. If you vomit or have diarrhea within 4 hours after taking your pill, follow the instructions in, “What to do if you miss pills.”
5. Missing pills can also cause spotting or light bleeding, even when you take the missed pills later. On the days you take 2 pills to make up for missed pills, you could also feel a little sick to your stomach.
6. If you have trouble remembering to take RIVELSA, talk to your healthcare provider about how to make pill-taking easier or about using another method of birth control.

Before you start taking RIVELSA

1. Decide what time of day you want to take your pill. It is important to take it at about the same time every day.
2. Look at your Extended-Cycle Tablet Dispenser. Your Extended-Cycle Tablet Dispenser consists of 3 trays with cards that hold 91 individually sealed pills (a 13-week or 91-day cycle). The 91 pills consist of 42 light pink tablets, each containing 0.15 mg of levonorgestrel and 0.02 mg ethinyl estradiol, 21 pink tablets containing 0.15 mg of levonorgestrel and 0.025 mg ethinyl estradiol, 21 purple tablets containing 0.15 mg of levonorgestrel and 0.03 mg ethinyl estradiol, and 7 yellow tablets containing 0.01 mg of ethinyl estradiol.
  Tray 1 contains 4 rows of 7 light pink pills.
  Tray 2 contains 2 rows of 7 light pink pills (a total of 14 light pink pills) followed by 2 rows of 7 pink pills (a total of 14 pink pills).
  Tray 3 contains 1 row of 7 pink pills, followed by three rows of 7 purple pills (a total of 21 purple pills), followed by the last row, which contains 7 yellow pills.
3. Also find:
  - Where on the first tray in the pack to start taking pills (upper left corner at the start arrow) and
  - In what order to take the pills (follow the weeks and arrow).
4. Be sure you have another kind of birth control (such as condoms and spermicide) ready at all times, to use as a backup in case you miss pills.

When to start RIVELSA

1. Take the first light pink pill on the Sunday after your period starts, even if you are still bleeding. If your period begins on Sunday, start the first light pink pill that same day.
2. Use another method of birth control (such as condoms and spermicide) as a backup method if you have sex anytime from the Sunday you start your first light pink pill until the next Sunday (first 7 days).

If you are switching from another birth control method:

If you have been using a different hormonal method of birth control (such as a different pill, the “patch,” or the “vaginal ring”), wait for your next period and begin taking RIVELSA on the Sunday after your period starts as instructed in steps 1 and 2 in, “When to start RIVELSA” above. You need to use another method of birth control (such as condoms and spermicide) each time you have sex after stopping your old method of birth control until you have taken RIVELSA for 7 days.

If you have recently given birth and have not yet had a period, use another method of birth control if you have sex (such as condoms and spermicide) as a backup method until you have taken RIVELSA for 7 days.

How to take RIVELSA

1. Take one pill at the same time every day until you have taken the last pill in the Extended-Cycle Tablet Dispenser.
  - Do not skip pills even if you are experiencing spotting or bleeding or feel sick to your stomach (nausea).
  - Do not skip pills even if you do not have sex very often.
  - Do not skip the yellow pills because they are not placebo pills (“sugar pills”). They contain ethinyl estradiol.
2. When you finish a tablet dispenser
  - After taking the last yellow pill, start taking the first light pink pill from a new Extended-Cycle Tablet Dispenser the very next day (this should be on a Sunday) regardless of when your period started.
3. If you miss your scheduled period when you are taking the yellow pills, contact your healthcare provider because you may be pregnant. If you are pregnant, you should stop taking RIVELSA.

What to do if you miss pills

If you MISS 1 light pink, pink or purple pill:

1. Take it as soon as you remember. Take the next pill at your regular time. This means you may take 2 pills in 1 day.
2. You do not need to use a backup birth control method if you have sex.

If you MISS 2 light pink, pink or purple pills in a row:

1. Take 2 pills on the day you remember, and 2 pills the next day.
2. Then take 1 pill a day until you finish the pack.
3. You could become pregnant if you have sex in the 7 days after you miss two pills. You MUST use another birth control method (such as condoms and spermicide) as a backup for the 7 days after you restart your pills.

If you MISS 3 OR MORE light pink, pink or purple pills in a row:

1. Do not take the missed pills. Keep taking 1 pill every day as indicated on the pack until you have completed all of the remaining pills in the pack. For example: If you resume taking the pill on Thursday, take the pill under “Thursday” and do not take the missed pills. You may experience bleeding during the week following the missed pills.
2. You could become pregnant if you have sex during the days of missed pills or during the first 7 days after restarting your pills.
3. You MUST use a non-hormonal birth control method (such as condoms and spermicide) as a backup when you miss pills and for the first 7 days after you restart your pills. If you do not have your period when you are taking the yellow pills, call your healthcare provider because you may be pregnant.

If you MISS ANY of the 7 yellow pills:

1. Throw away the missed pills.
2. Take the next scheduled pill at the scheduled time.
3. You do not need a backup method of birth control.

Finally, if you are still not sure what to do about the pills you have missed

1. Use a backup method anytime you have sex.
2. Keep taking one pill each day until you contact your healthcare provider.

If you have any questions or are unsure about the information in this leaflet, call your healthcare provider.

Manufactured for:
Teva Pharmaceuticals
Parsippany, NJ 07054

This Patient Information and Instructions for Use has been approved by the U.S. Food and Drug Administration.

Revised: 10/2024

RIVPL-005

©2024 Teva Pharmaceuticals, Inc.

Package/Label Display Panel, Part 1 of 2

NDC 0093-6031-82

RIVELSA™

(levonorgestrel/ethinyl estradiol) tablets

0.15 mg/0.02 mg, 0.15 mg/0.025 mg,

0.15 mg/0.03 mg

(ethinyl estradiol) tablets

0.01 mg

Usual Dosage:

One tablet daily for 91 consecutive days in the following order: 42 light pink tablets each

containing 0.15 mg levonorgestrel and 0.02 mg ethinyl estradiol, 21 pink tablets each

containing 0.15 mg of levonorgestrel and 0.025 mg ethinyl estradiol, and 21 purple

tablets each containing 0.15 mg of levonorgestrel and 0.03 mg ethinyl estradiol, and

7 yellow tablets each containing 0.01 mg of ethinyl estradiol.

Pharmacist: Dispense patient information with each prescription.

Rx only

2 Extended-Cycle Tablet Dispensers,

91 Tablets Each

TEVA

Package/Label Display Panel, Part 2 of 2

NDC 0093-6031-82

RIVELSA™

(levonorgestrel/ethinyl estradiol) tablets

0.15 mg/0.02 mg, 0.15 mg/0.025 mg,

0.15 mg/0.03 mg

(ethinyl estradiol) tablets

0.01 mg

Usual Dosage:

One tablet daily for 91 consecutive days in the following order: 42 light pink tablets each

containing 0.15 mg levonorgestrel and 0.02 mg ethinyl estradiol, 21 pink tablets each

containing 0.15 mg of levonorgestrel and 0.025 mg ethinyl estradiol, and 21 purple

tablets each containing 0.15 mg of levonorgestrel and 0.03 mg ethinyl estradiol, and

7 yellow tablets each containing 0.01 mg of ethinyl estradiol.

Pharmacist: Dispense patient information with each prescription.

Rx only

2 Extended-Cycle Tablet Dispensers,

91 Tablets Each

TEVA